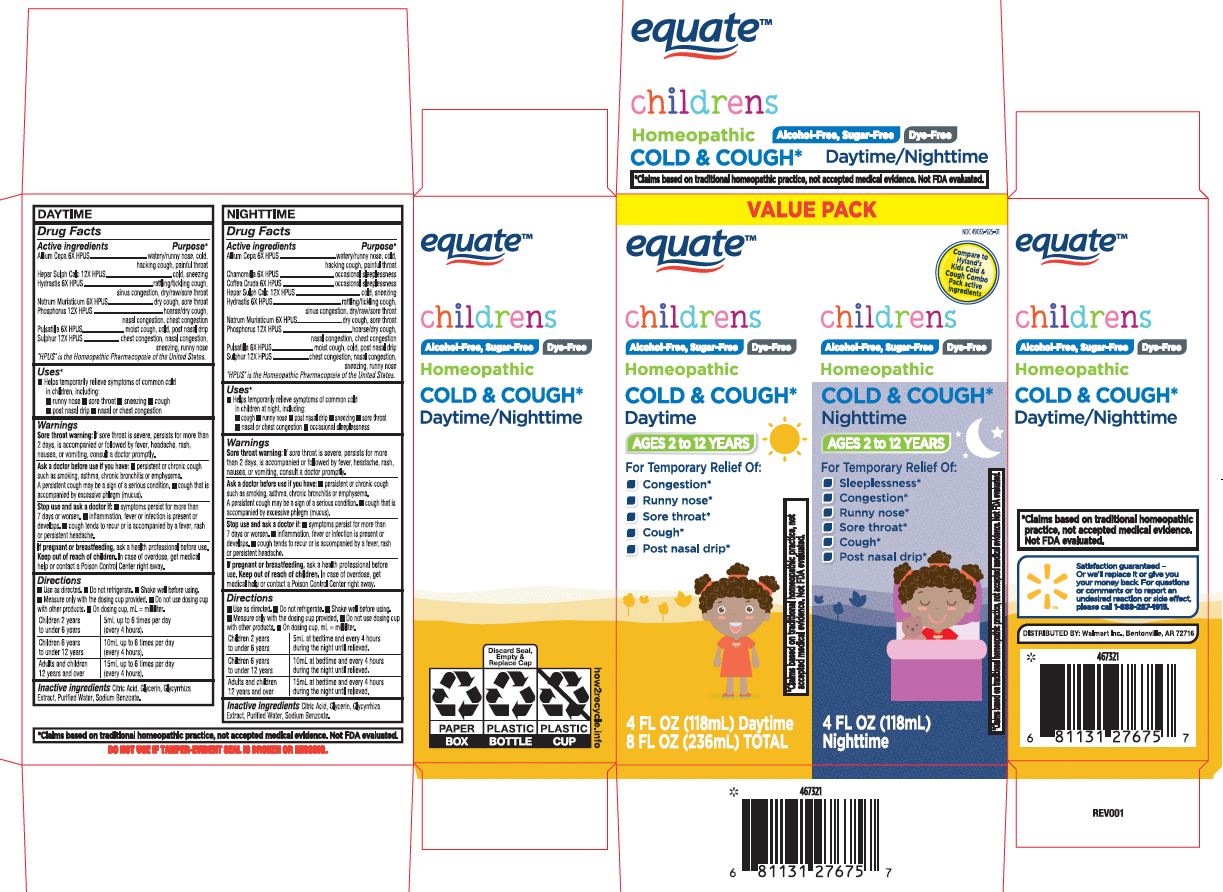 DRUG LABEL: Childrens Cold and Cough Day and Night Twin Pack
NDC: 49035-925 | Form: KIT | Route: ORAL
Manufacturer: Wal-Mart Stores, Inc
Category: homeopathic | Type: HUMAN OTC DRUG LABEL
Date: 20251219

ACTIVE INGREDIENTS: ONION 6 [hp_X]/1 mL; ARABICA COFFEE BEAN 6 [hp_X]/1 mL; CALCIUM SULFIDE 12 [hp_X]/1 mL; PHOSPHORUS 12 [hp_X]/1 mL; ANEMONE PULSATILLA 6 [hp_X]/1 mL; SODIUM CHLORIDE 6 [hp_X]/1 mL; MATRICARIA CHAMOMILLA 6 [hp_X]/1 mL; SULFUR 12 [hp_X]/1 mL; GOLDENSEAL 6 [hp_X]/1 mL; PHOSPHORUS 12 [hp_X]/1 mL; ANEMONE PULSATILLA 6 [hp_X]/1 mL; GOLDENSEAL 6 [hp_X]/1 mL; SODIUM CHLORIDE 6 [hp_X]/1 mL; SULFUR 12 [hp_X]/1 mL; ONION 6 [hp_X]/1 mL; CALCIUM SULFIDE 12 [hp_X]/1 mL
INACTIVE INGREDIENTS: GLYCYRRHIZA GLABRA; WATER; CITRIC ACID MONOHYDRATE; GLYCERIN; SODIUM BENZOATE; GLYCYRRHIZA GLABRA; CITRIC ACID MONOHYDRATE; WATER; GLYCERIN; SODIUM BENZOATE

Equate Children’s Cold & Cough Day & Night Value Pack

DAYTIME

Drug Facts

ACTIVE INGREDIENT

Active ingredients | Purpose
Allium Cepa 6X HPUS | watery/runny nose, cold, hacking cough, sore throat
Hepar Sulph Calc 12X HPUS | cold, sneezing
Hydrastis 6X HPUS | rattling/tickling cough, sinus congestion, dry/raw/sore throat
Natrum Muriaticum 6X HPUS | dry cough, sore throat
Phosphorus 12X HPUS | hoarse/dry cough, nasal congestion, chest congestion
Pulsatilla 6X HPUS | moist cough, cold, nasal congestion
Sulphur 12X HPUS | chest congestion, nasal congestion, sneezing, runny nose

“HPUS” indicates that the active ingredients are in the official Homeopathic Pharmacopœia of the United States.

Uses

Temporarily relieves the symptoms of the common cold including nasal and chest congestion, runny nose, sore throat, sneezing and cough.

Warnings

PREGNANCY OR BREAST FEEDING

As with any drug, ask a doctor before use if pregnant or breast-feeding

ASK DOCTOR

Consult a physician if:

- Symptoms persist for more than 7 days or worsen
- Inflammation, fever or infection develops
- Symptoms are accompanied by a high fever (over 101°F)
- Cough tends to recur or is accompanied by a high fever, rash or persistent headache

KEEP OUT OF REACH OF CHILDREN

Keep this and all medications out of the reach of children.

Do not use this product for persistent or chronic cough such as asthma, smoking or emphysema or if cough is accompanied by excessive mucus, unless directed by a licensed medical professional.

A persistent cough may be a sign of a serious condition.

Sore throat warning: Severe or persistent sore throat or sore throat accompanied by high fever, headache, nausea and vomiting may be serious. Consult a doctor promptly.

DO NOT USE

In case of emergency or accidental overdose,

contact a medical professional or Poison Control

Center immediately.

Directions

- Shake well before using.
- Measure only with the dosing cup provided.
- Do not use dosing cup with other products.
- On dosing cup, mL = milliliter.

Drug Facts (continued)

Children 2 years; to under 6 years | 5mL up to 6 times; per day (every 4 hours)
Children 6 years; to under 12 years | 10mL up to 6 times; per day (every 4 hours)
Adults and children; 12 years and over | 15mL up to 6 times; per day (every 4 hours)

Other information

- Do not use if imprinted "SEALED FOR YOUR PROTECTION" tamper-evident bottle cap band is broken or missing.
- The inner packaged bottle is child-resistant.
- Store at room temperature.
- Do not refrigerate.

Inactive ingredients

Citric Acid, Glycerin, Glycyrrhiza Extract, Purified Water, Sodium Benzoate.

NIGHTTIME

Drug Facts

ACTIVE INGREDIENT

Active ingredients | Purpose
Allium Cepa 6X HPUS | watery/runny nose, cold, hacking cough, sore throat
Chamomilla 6X HPUS | sensitive, irritable, fussy, nocturnal occasional sleeplessness
Coffea Cruda 6X HPUS | occasional sleeplessness, restlessness
Hepar Sulph Calc 12X HPUS | cold, sneezing
Hydrastis 6X HPUS | rattling, tickling cough, sinus congestion, dry/raw/sore throat
Natrum Muriaticum 6X HPUS | dry cough, sore throat
Phosphorus 12X HPUS | hoarse/dry cough, nasal congestion, chest congestion
Pulsatilla 6X HPUS | moist cough, cold, nasal congestion
Sulphur 12X HPUS | chest congestion, nasal congestion, sneezing, runny nose

“HPUS” indicates that the active ingredients are in the official Homeopathic Pharmacopœia of the United States.

Uses

Temporarily relieves the symptoms of the common cold including cough, runny nose, sneezing, nasal and chest congestion, and sore throat with accompanying occasional sleeplessness.

Warnings

PREGNANCY OR BREAST FEEDING

As with any drug, ask a doctor before use if pregnant or breast-feeding.

Consult a physician if:

- Symptoms persist for more than 7 days or worsen
- Inflammation, fever or infection develops



Drug Facts (continued)

- Symptoms are accompanied by a high fever (over 101°F)
- Cough tends to recur or is accompanied by a high fever, rash or persistent headache

KEEP OUT OF REACH OF CHILDREN

Keep this and all medications out of the reach of

children.

Do not use this product for persistent or chronic

cough such as asthma, smoking or emphysema or if

cough is accompanied by excessive mucus, unless

directed by a licensed medical professional.

A persistent cough may be a sign of a serious

condition.

DO NOT USE

Sore throat warning: Severe or persistent sore throat or sore throat accompanied by high fever, headache, nausea and vomiting may be serious. Consult a doctor promptly.

In case of emergency or accidental overdose, contact a medical professional or Poison Control Center immediately.

Directions

- Shake well before using.
- Measure only with the dosing cup provided.
- Do not use dosing cup with other products.
- On dosing cup, mL = milliliter.

Children 2 years to under 6 years | 5mL at bedtime and every 4 hours during the night; or as necessary
Children 6 years to under 12 years | 10mL at bedtime and every 4 hours during the night or as necessary
Adults and children 12 years and over | 15mL at bedtime and every 4 hours during the night or as necessary

Other information

- Do not use if imprinted "SEALED FOR YOUR PROTECTION" tamper-evident bottle cap band is broken or missing.
- The inner packaged bottle is child-resistant.
- Store at room temperature.
- Do not refrigerate.

Inactive ingredients

Citric Acid, Glycerin, Glycyrrhiza Extract, Purified Water, Sodium Benzoate.

*Claims based on traditional homeopathic

practice, not accepted medical evidence.

Not FDA evaluated.

Dosage and Administration

 Directions

Shake well before using.

 Measure only with the dosing cup provided.

 Do not use dosing cup with other products.

 On dosing cup, mL = milliliter.

Removed 2 teaspoon

Primary Principal Display Panel - Children's Cold & Cough Day & Night Value Pack

VALUE PACK

NDC 49035-95-01

Equate™

Compare to

Hyland’s 4 Kids

Cold ‘n Cough Day

& Night Value Pack

active ingredients

Children's

Alcohol-Free, Sugar-Free Dye-Free

Homeopathic

Cold & Cough*

Daytime

Ages 2 to12 years

For Temporary Relief of:

- Nasal congestion
- Runny nose
- Sore throat
- Sneezing
- Cough

*Claims based on traditional homeopathic practice, not accepted medical evidence. Not FDA evaluated.

4 FL OZ (118mL) Daytime

8 FL OZ (236mL) TOTAL

Children's

Alcohol-Free, Sugar-Free Dye-Free

Homeopathic

Cold & Cough*

Nighttime

Ages 2 to12 years

For Temporary Relief of:

- Chest congestion
- Occasional sleeplessness
- Runny nose
- Sore throat
- Sneezing
- Cough

*Claims based on traditional homeopathic practice, not accepted medical evidence. Not FDA evaluated.

4 FL OZ (118mL) Nighttime